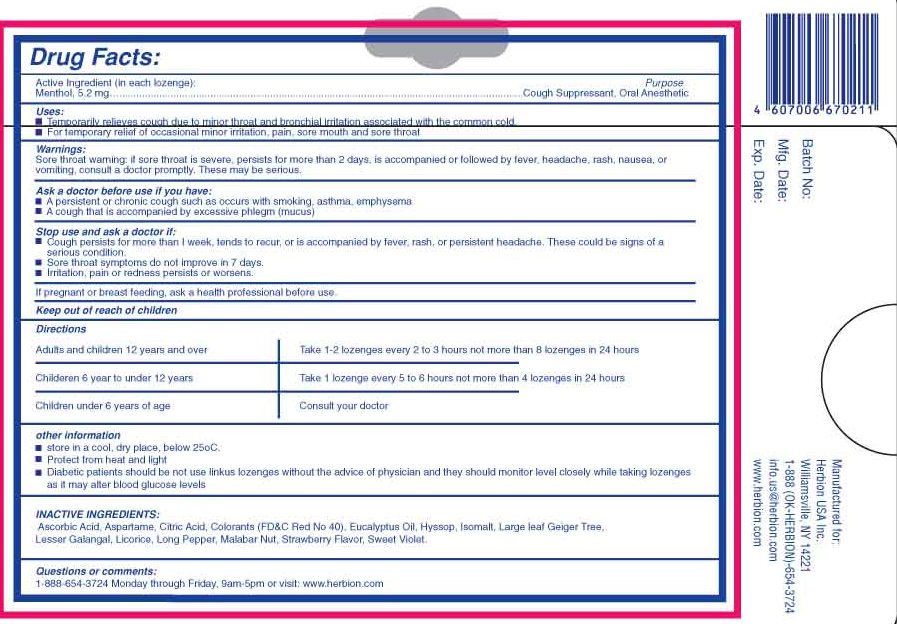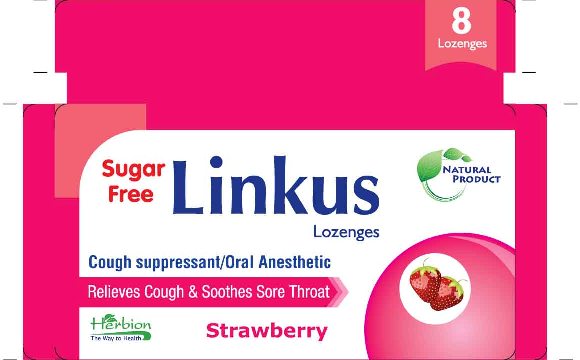 DRUG LABEL: Linkus Lozenges
NDC: 44237-006 | Form: LOZENGE
Manufacturer: Herbion Pakistan (Pvt.) Ltd.
Category: otc | Type: HUMAN OTC DRUG LABEL
Date: 20100308

ACTIVE INGREDIENTS: MENTHOL 5 mg/1 1

ACTIVE INGREDIENT

Menthol 5.2mg

PURPOSE

Cough Suppresant, Oral Anesthetic

Uses:

- Temporarily relieves cough due to minor throat and bronchial irritation associated with the common cold
- For temporary relief of occasional minor irritation, pain, sore mouth and sore throat

WARNINGS

Sore throat warning: if sore throat is severe, persists for more than 2 days, is accompanied or followed by fever, headache, rash, nausea, or vomitting, consult a doctor promptly. These may be serious.

Stop use and ask a doctor if:

- Cough persists for more than 1 week, tends to recur, or is accompanied by fever, rash, or persisted headache. These could be signs of a serious condition
- Sore throat symptoms do not improve in 7 days
- Irritation, pain or redness persists or worsens

Ask a doctor before use if you have:

- A persistent or chronic cough such as occurs with smoking, asthma, emphysema
- A cough that is accompanied by excessive phlegm (mucus)

PREGNANCY OR BREAST FEEDING

If pregnant or breast feeding ask a health professional before use.

Keep out of reach of children.

Directions

Adults and children 12 years and over Take 1-2 lozenges every 2 to 3 hours not more than 8 lozenges in 24 hours
Children 6 years to under 12 years Take 1 lozenge every 5 to 6 hours not more than 4 lozenges in 24 hours
Children under 6 years of age Consult your doctor

Other Information:

- store in a cool, dry place, below 25 degrees C
- Protect from heat and light
- Diabetic patients should not use linkus lozenges without the advice of physician and they should monitor glucose levels closely while taking lozenges as it may alter blood glucose levels

Manufactured for:
Herbion USA Inc.
Williamsville NY 14221
1-888-(OK-HERBION)-654-3724
info.us@herbion.com
www.herbion.com

INACTIVE INGREDIENT

Ascorbic Acid, Aspartame, Colorants Red No. 40, Eucalyptus Oil, Hyssop, Large leaf Geiger Tree, Lesser Galangal, Licorice, Liquid Glucose, Long Pepper, Malabar Nut, Strawberry Flavor, Sweet Violet

Questions or comments:

1-888-654-3724 Monday thru Friday, 9am-5pm or visit www.Herbion.com

PACKAGE LABEL

Linkus Lozenges

Sugar Free

Cough Suppresant Oral Anesthetic

Relieves Cough and Soothes Sore Throat

Strawberry